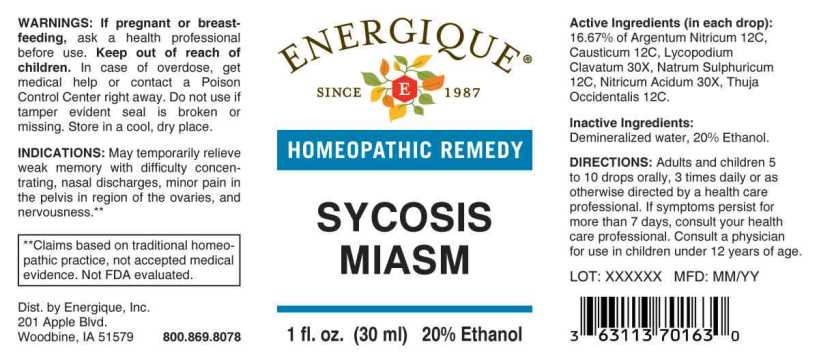 DRUG LABEL: Sycosis Miasm
NDC: 44911-0468 | Form: LIQUID
Manufacturer: Energique, Inc.
Category: homeopathic | Type: HUMAN OTC DRUG LABEL
Date: 20241030

ACTIVE INGREDIENTS: NITRIC ACID 30 [hp_X]/1 mL; LYCOPODIUM CLAVATUM SPORE 30 [hp_X]/1 mL; SILVER NITRATE 12 [hp_C]/1 mL; CAUSTICUM 12 [hp_C]/1 mL; SODIUM SULFATE 12 [hp_C]/1 mL; THUJA OCCIDENTALIS LEAFY TWIG 12 [hp_C]/1 mL
INACTIVE INGREDIENTS: WATER; ALCOHOL

DRUG FACTS:

ACTIVE INGREDIENTS:

(in each drop): 16.67% of Argentum Nitricum 12C, Causticum 12C, Lycopodium Clavatum 30X, Natrum Sulphuricum 12C, Nitricum Acidum 30X, Thuja Occidentalis 12C.

INDICATIONS:

May temporarily relieve weak memory with difficulty concentrating, nasal discharges, minor pain in the pelvis region of the ovaries, and nervousness.**

**Claims based on traditional homeopathic practice, not accepted medical evidence. Not FDA evaluated.

WARNINGS:

If pregnant or breastfeeding, ask a health professional before use.

Keep out of reach of children. In case of overdose, get medical help or contact a Poison Control Center right away.

Do not use if tamper evident seal is broken or missing.

Store in a cool, dry place.

Keep out of reach of children. In case of overdose, get medical help or contact a Poison Control Center right away.

DIRECTIONS:

Adults and children 5 to 10 drops orally, 3 times daily or as otherwise directed by a health care professional. If symptoms persist, consult your health care professional. Consult a physician for use in children under 12 years of age.

INDICATIONS:

May temporarily relieve weak memory with difficulty concentrating, nasal discharges, minor pain in the pelvis region of the ovaries, and nervousness.**

**Claims based on traditional homeopathic practice, not accepted medical evidence. Not FDA evaluated.

INACTIVE INGREDIENTS:

Demineralized water, 20% Ethanol.

QUESTIONS:

Dist. by Energique, Inc.

201 Apple Blvd.

Woodbine, IA 51579 800.868.8078

PACKAGE LABEL DISPLAY:

ENERGIQUE

SINCE 1987

HOMEOPATHIC REMEDY

SYCOSIS

MIASM

1 fl. oz. (30 ml)